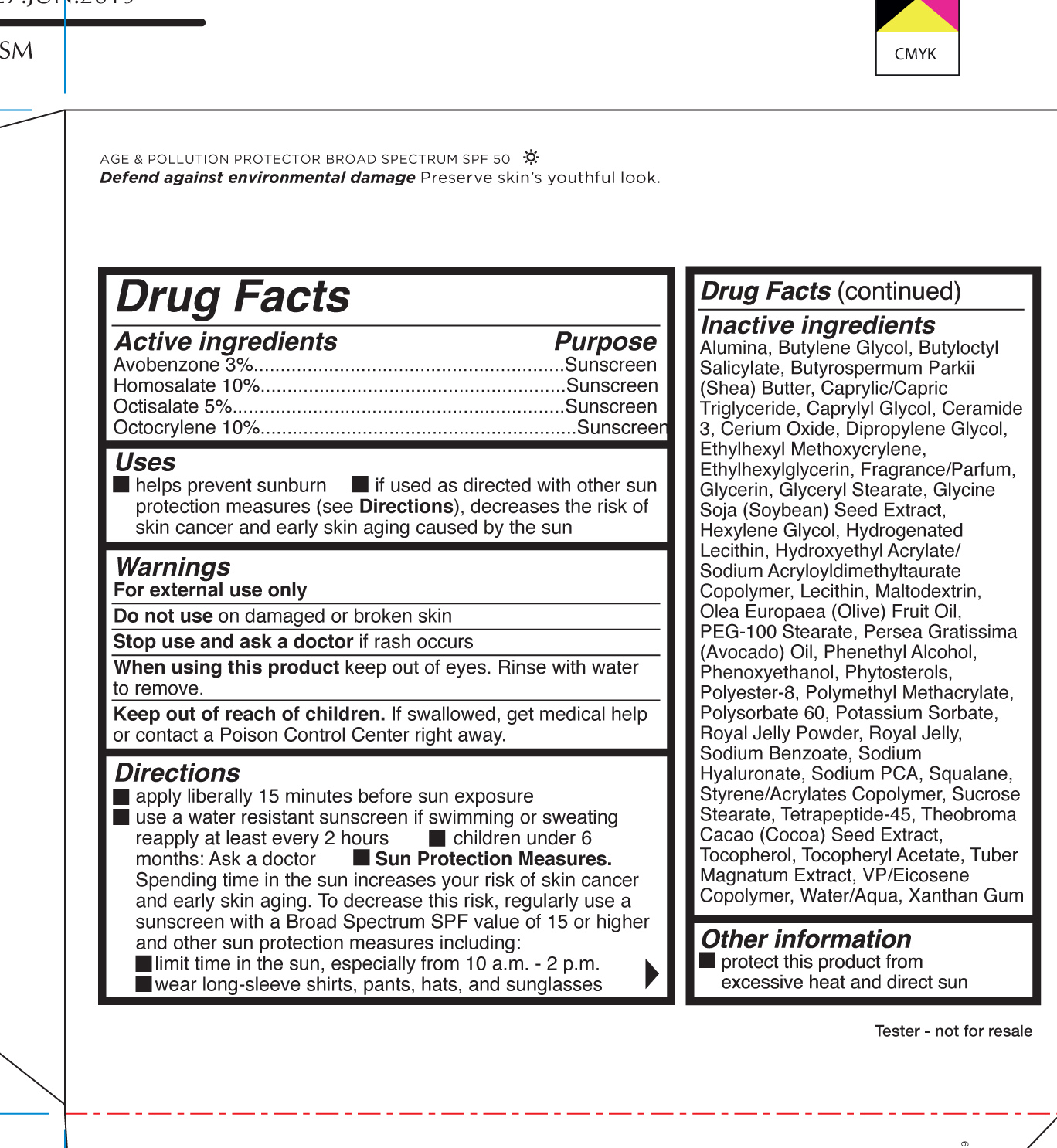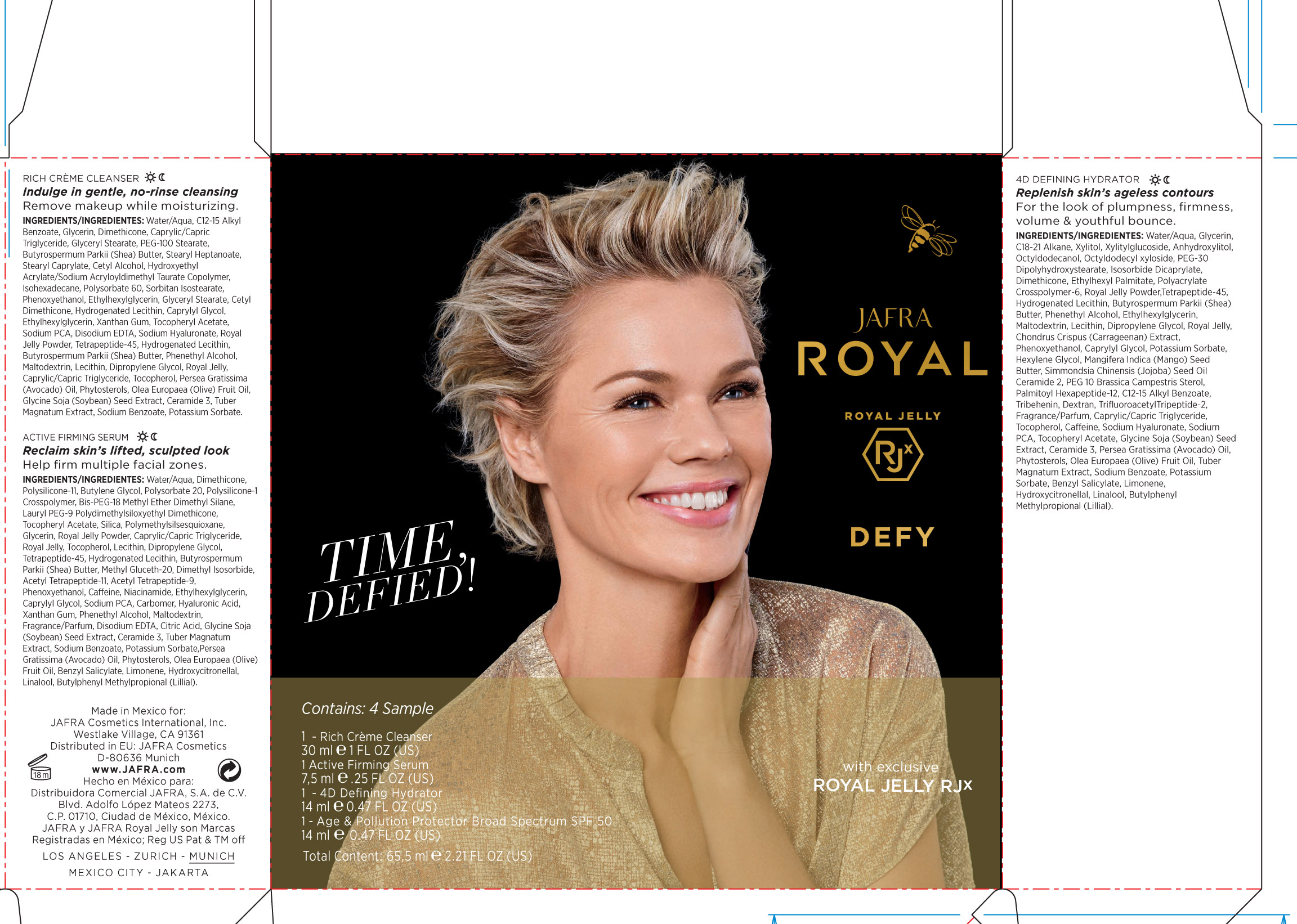 DRUG LABEL: Royal Jelly Defy Age and pollution protector Broad Spectrum SPF 50
NDC: 68828-410 | Form: KIT | Route: TOPICAL
Manufacturer: Jafra cosmetics International
Category: otc | Type: HUMAN OTC DRUG LABEL
Date: 20190711

ACTIVE INGREDIENTS: AVOBENZONE 3 g/100 mL; HOMOSALATE 10 g/100 mL; OCTISALATE 5 g/100 mL; OCTOCRYLENE 10 g/100 mL
INACTIVE INGREDIENTS: CERIC OXIDE; ALUMINUM OXIDE; VINYLPYRROLIDONE/EICOSENE COPOLYMER; GLYCERIN; ETHYLHEXYLGLYCERIN; ETHYLHEXYL METHOXYCRYLENE; BUTYLOCTYL SALICYLATE; PHENYLETHYL ALCOHOL; POLYESTER-8 (1400 MW, CYANODIPHENYLPROPENOYL CAPPED); CERAMIDE NP; BUTYLENE GLYCOL; POLYSORBATE 60; PHENOXYETHANOL; DIPROPYLENE GLYCOL; POTASSIUM SORBATE; HYDROGENATED SOYBEAN LECITHIN; AVOCADO OIL; POLY(METHYL METHACRYLATE; 450000 MW); WATER; COCOA; GLYCERYL MONOSTEARATE; PEG-100 STEARATE; HEXYLENE GLYCOL; HYDROXYETHYL ACRYLATE/SODIUM ACRYLOYLDIMETHYL TAURATE COPOLYMER (100000 MPA.S AT 1.5%); LECITHIN, SOYBEAN; MALTODEXTRIN; SQUALANE; TOCOPHEROL; XANTHAN GUM; MEDIUM-CHAIN TRIGLYCERIDES; CAPRYLYL GLYCOL; HYALURONATE SODIUM; SOYBEAN; SODIUM BENZOATE; ROYAL JELLY; SODIUM PYRROLIDONE CARBOXYLATE; .ALPHA.-TOCOPHEROL ACETATE; SHEA BUTTER; OLIVE OIL

Royal Jelly Defy Age and pollution protector Broad Spectrum SPF 50

Active Ingredients Purpose

Avobenzone 3% Sunscreen

Homosalate 10% Sunscreen

Octisalate 5% Sunscreen

Octocrylene 10% Sunscreen

Uses

helps prevent sunburn

if used as directed with other sun protection measures (see Directions), decreases the risk of skin cancer and early skin aging caused by the sun

Keep out of reach of children. If swallowed, get medical help or contact a Poison Control Center right away

Stop use and ask a doctor if rash occurs

Warnings

For external use only

Do not use on damaged or broken skin

When using this product keep out of eyes. Rinse with water to remove.

Directions

Apply generously and evenly 15 minutes before sun exposure

Use a water-resistant sunscreen if swimming or sweating

Reapply at least every 2 hours.

Sun Protection Measures Spending time in the sun increases your risk of

skin cancer and early skin aging. To decrease this risk, regularly use a

sunscreen with a Broad-Spectrum SPF value of 15 or higher and other sun

protection measures including:

• limit your time in the sun, especially from 10 a.m. – 2 p.m.

• wear long-sleeved shirts, pants, hats, and sunglasses

• Children under 6 months of age: ask a doctor.

Inactive ingredients

Alumina, Butylene Glycol, Butyloctyl Salicylate, Butyrospermum Parkii (Shea) Butter, Caprylic/Capric Triglyceride, Caprylyl Glycol, Ceramide 3, Cerium Oxide, Dipropylene Glycol, Ethylhexyl Methoxycrylene, Ethylhexylglycerin, Fragrance/Parfum, Glycerin, Glyceryl Stearate, Glycine Soja (Soybean) Seed Extract, Hexylene Glycol, Hydrogenated Lecithin, Hydroxyethyl Acrylate/ Sodium Acryloyldimethyltaurate Copolymer, Lecithin, Maltodextrin, Olea Europaea (Olive) Fruit Oil, PEG-100 Stearate, Persea Gratissima (Avocado) Oil, Phenethyl Alcohol, Phenoxyethanol, Phytosterols, Polyester-8, Polymethyl Methacrylate, Polysorbate 60, Potassium Sorbate, Royal Jelly Powder, Royal Jelly, Sodium Benzoate, Sodium Hyaluronate, Sodium PCA, Squalane, Styrene/Acrylates Copolymer, Sucrose Stearate, Tetrapeptide-45, Theobroma Cacao (Cocoa) Seed Extract, Tocopherol, Tocopheryl Acetate, Tuber Magnatum Extract, VP/Eicosene Copolymer, Water/Aqua, Xanthan Gum

PACKAGE LABEL

Jafra Royal Jelly

Defy

Age & Pollution Protector Broad Spectrum SFP 50

50 ml 1.7 Fl Oz